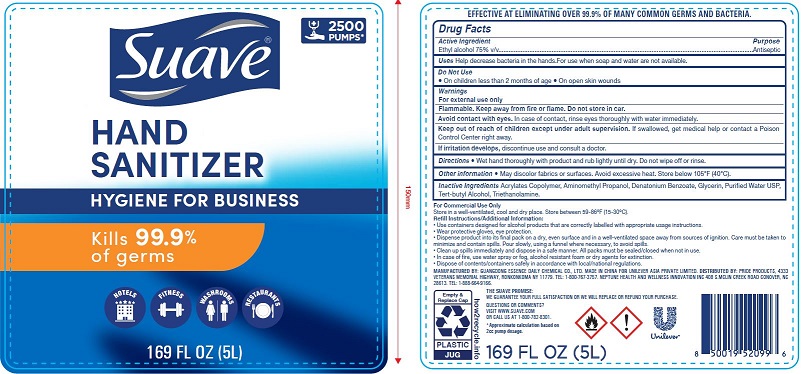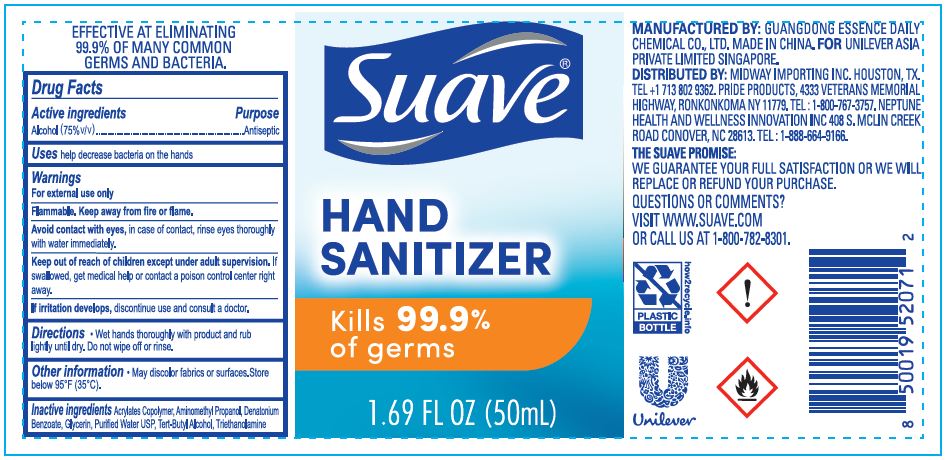 DRUG LABEL: Suave Hand Sanitizer Professional
NDC: 50069-110 | Form: GEL
Manufacturer: UNILEVER ASIA PRIVATE LIMITED
Category: otc | Type: HUMAN OTC DRUG LABEL
Date: 20201104

ACTIVE INGREDIENTS: ALCOHOL 75 mL/100 mL
INACTIVE INGREDIENTS: BUTYL ACRYLATE/METHYL METHACRYLATE/METHACRYLIC ACID COPOLYMER (18000 MW); AMINOMETHYLPROPANOL; DENATONIUM BENZOATE; GLYCERIN; WATER; TERT-BUTYL ALCOHOL; TROLAMINE

Suave Hand Sanitizer Professional - 75% Ethyl Alcohol

ACTIVE INGREDIENT

Ethyl alcohol 75% v/v

PURPOSE

ANTISEPTIC

USE

Hand sanitizer to help reduce bacteria that potentially can cause disease. For use when soap and water are not available.

WARNINGS

For External Use only. Highly flammable liquid and vapour. Keep away from/do not spray near heat, hot surfaces, sparks, electrical appliances, open flames and other ignition sources. Do not store in car. No smoking. Keep containers tightly closed.

Do Not Use

- On children less than 2 months of age
- On open skin wounds

When using this product keep out of eyes, ears, and mouth. In case of contact, rinse cautiously with water for several minutes. Remove contact lenses if present and easy to do. Continue rinsing. If eye irritation persists: Get medical advice/attention.

Stop use and ask a doctor if irritation or rash occurs. These may be signs of a serious condition.

Keep out of reach of children.

If swallowed, get medical help or contact a Poison Control Center right away.

Keep out of reach of children. Causes serious eye irritation. If swallowed, get medical help or contact Poison Control Center right away.

DIRECTIONS

- Wet hands thoroughly with product and rub lightly until dry. Do not wipe off or rinse.

OTHER INFORMATION

- Store between 15-30ºC (59-86ºF)
- Avoid freezing and excessive heat above 40ºC (104ºF)

INACTIVE INGREDIENTS

Acrylates Copolymer, Aminomethyl Propanol, Denatonium Benzoate, Glycerin, Purified Water USP, Tert-butyl Alcohol, Triethanolamine